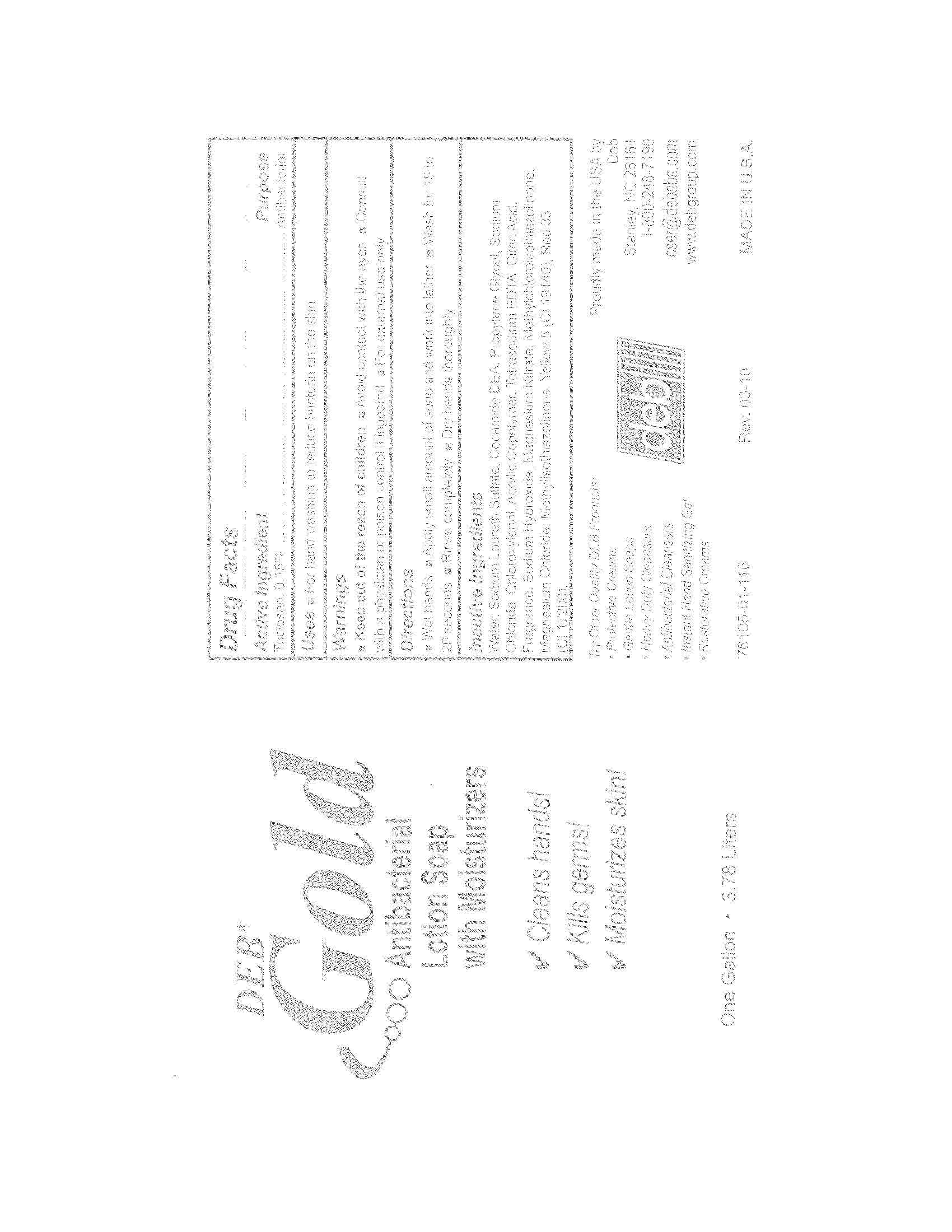 DRUG LABEL: Deb Gold
NDC: 11084-076 | Form: LIQUID
Manufacturer: Deb USA, Inc.
Category: otc | Type: HUMAN OTC DRUG LABEL
Date: 20100909

ACTIVE INGREDIENTS: TRICLOSAN 0.15 mL/100 mL
INACTIVE INGREDIENTS: WATER; SODIUM LAURETH SULFATE; COCO DIETHANOLAMIDE; PROPYLENE GLYCOL; SODIUM CHLORIDE; CHLOROXYLENOL; EDETATE SODIUM; ANHYDROUS CITRIC ACID; SODIUM HYDROXIDE; FD&C YELLOW NO. 5; D&C RED NO. 33; METHYLCHLOROISOTHIAZOLINONE; METHYLISOTHIAZOLINONE; MAGNESIUM NITRATE; MAGNESIUM CHLORIDE

Drug Facts

Active Ingredient

Triclosan, 0.15%

Purpose

Antibacterial

Uses

For handwashing to reduce bacteria on the skin

Warnings

For external use only

Avoid contact with the eyes

Keep out of reach of children

Consult a physician or poison control center if ingested

Directions

Wet hands

Apply small amount of soap and work into lather

Wash for 15 to 20 seconds

Rinse completely

Dry hands thoroughly

Inactive Ingredients

Water, Sodium Laureth Sulfate, Cocamide DEA, Propylene Glycol, Sodium Chloride, Chloroxylenol. Acrylic Copolymer, Tetrasodium EDTA, Citric Acid, Fragrance, Sodium Hydroxide, Magnesium Nitrate, Methylchloroisothiazolinone, Magnesium Chloride, Methylisothiazolinone, Yellow 5 (C! 19140), Red 33 (CI 17200).

PACKAGE LABEL

DEB

GOLD

Antibacterial Lotion Soap with Moisturizers

Cleans hands!

Kills germs!

Moisturizes skin!

One Gallon 3.78 Liters

76105-01-116

MADE IN U.S.A.